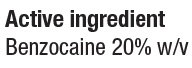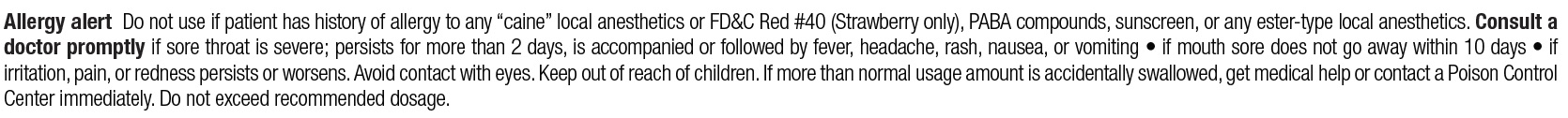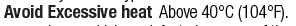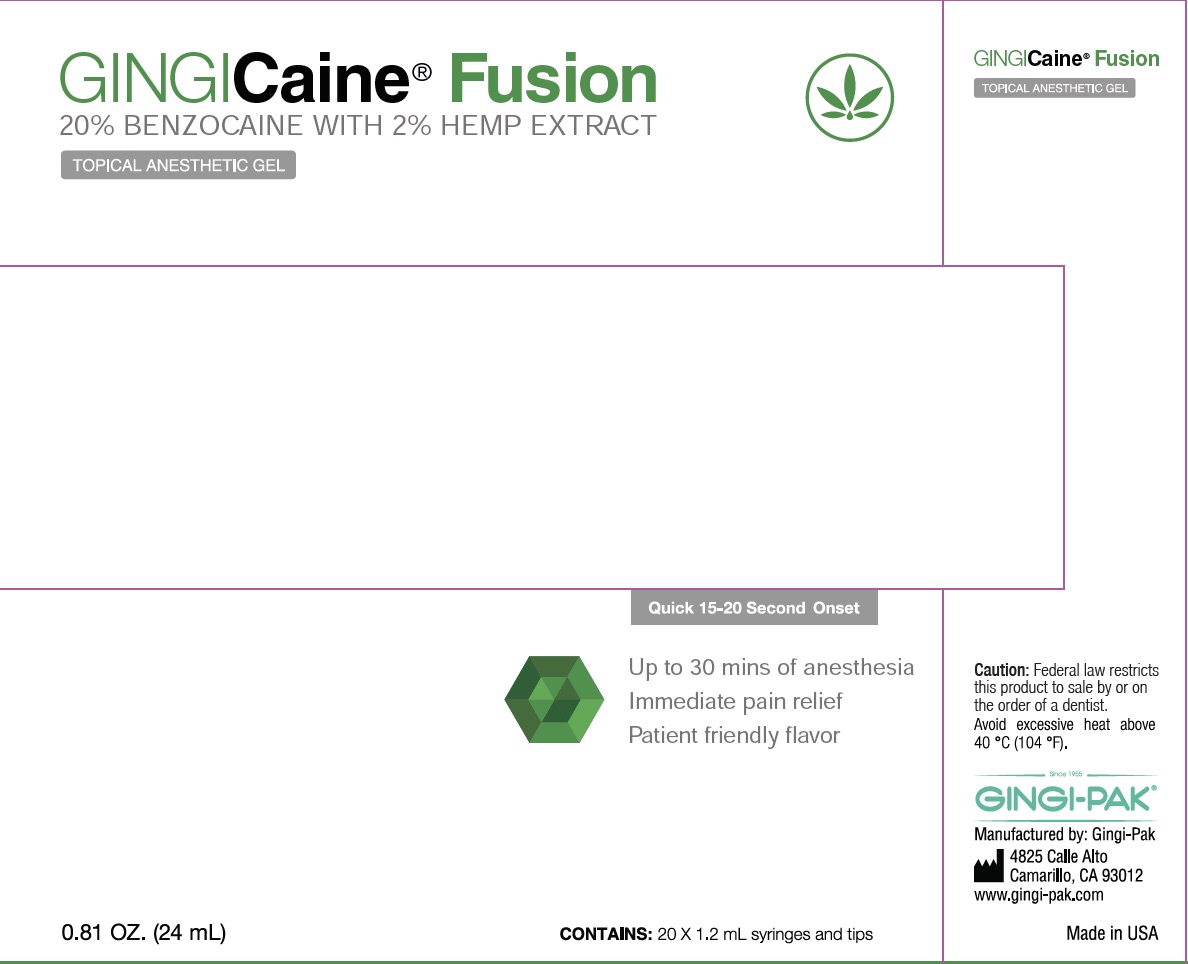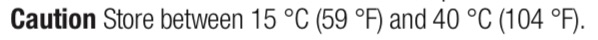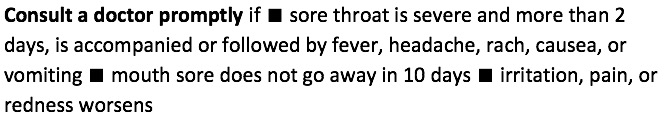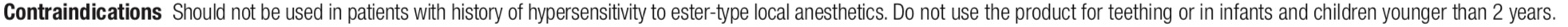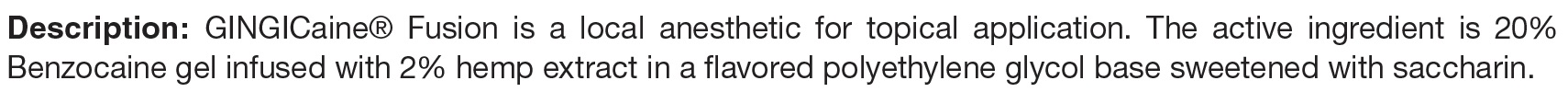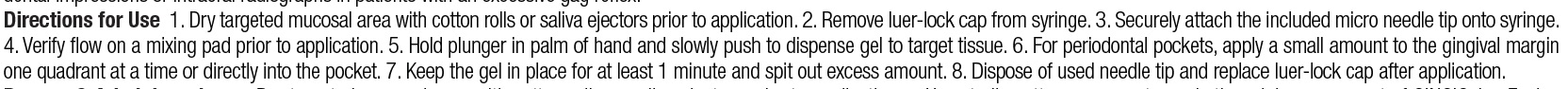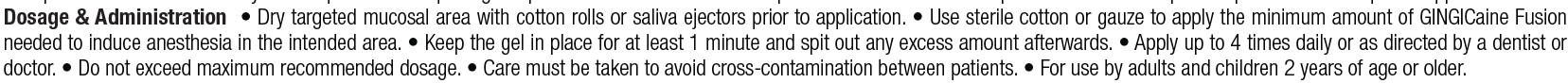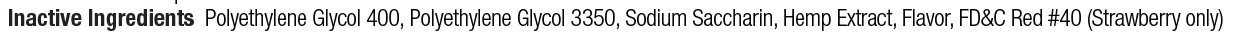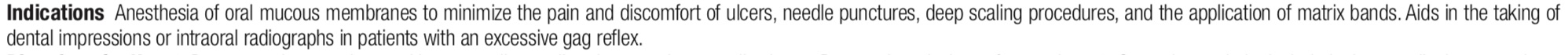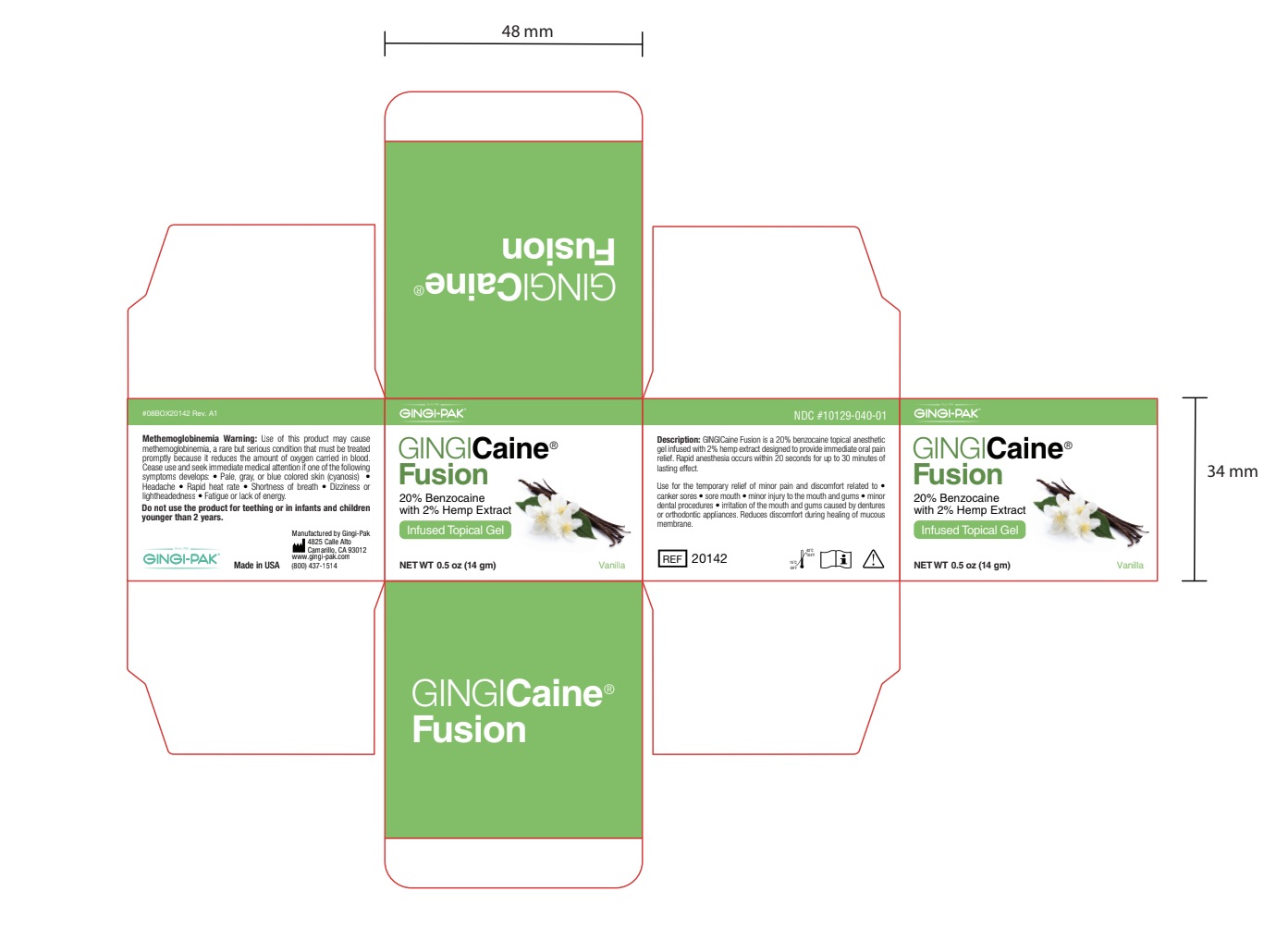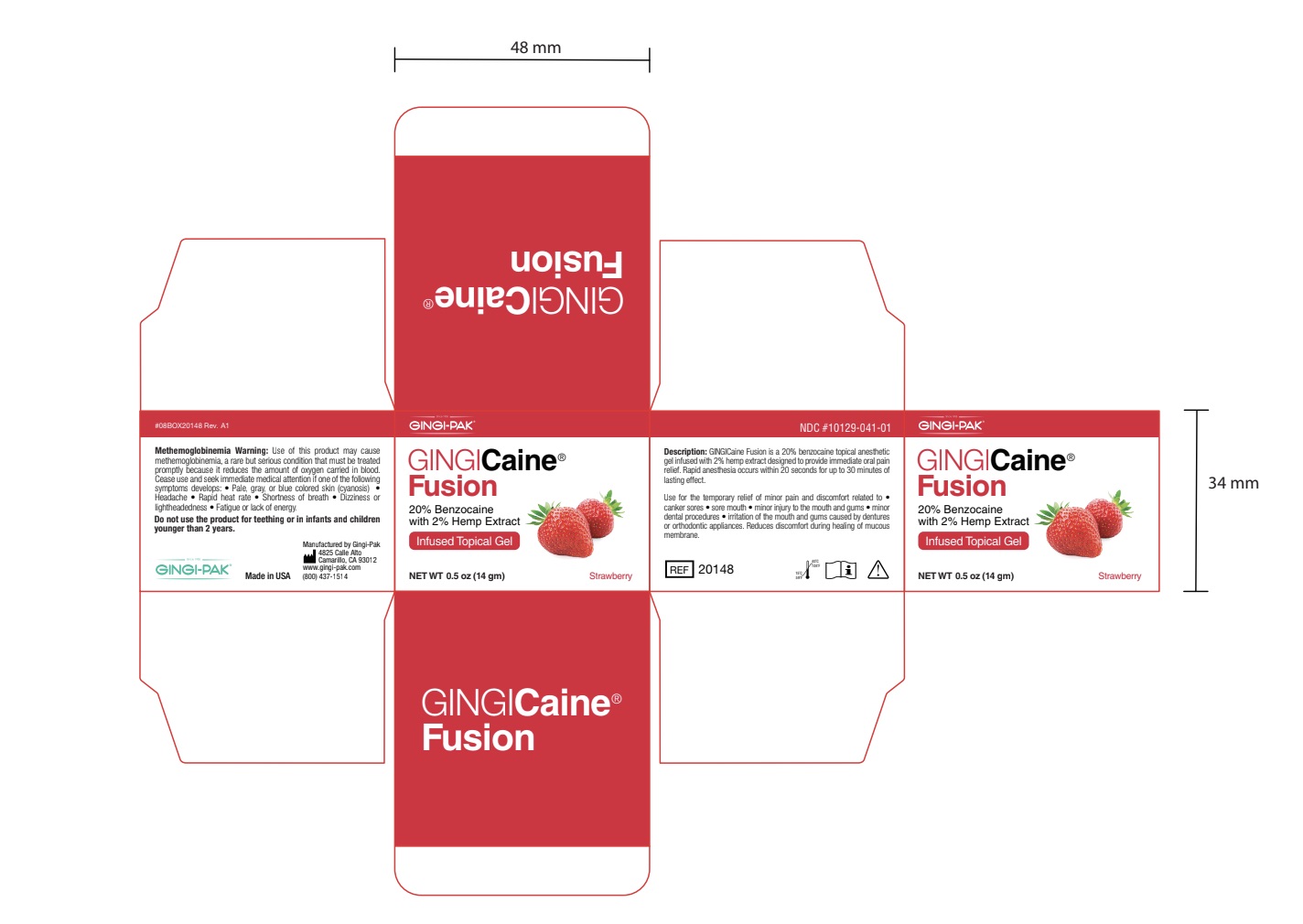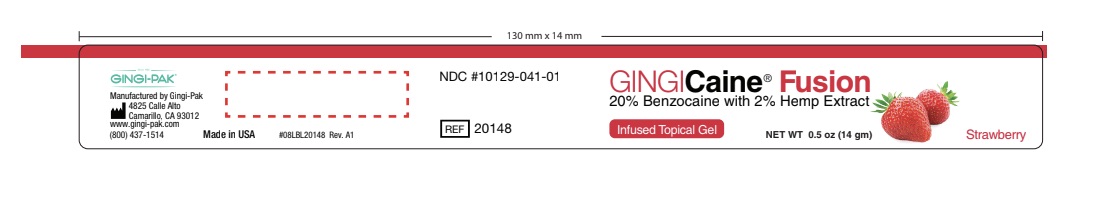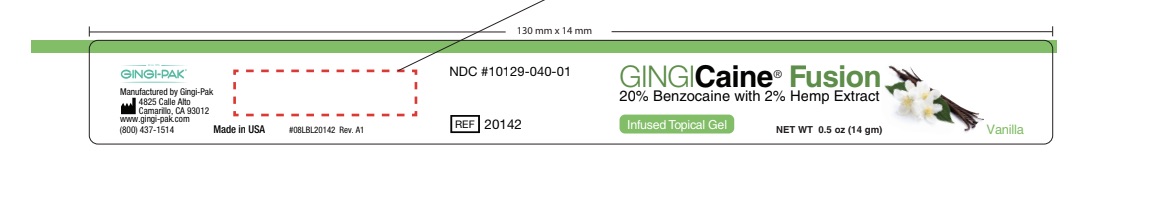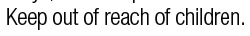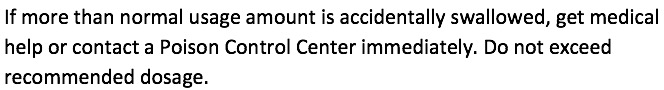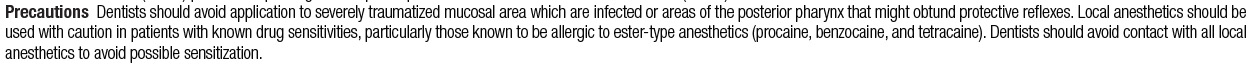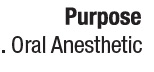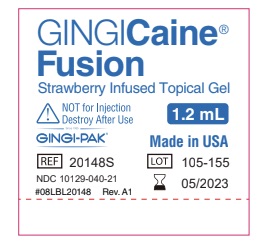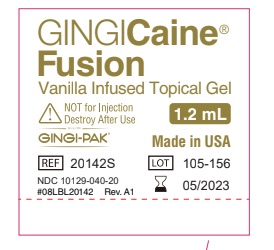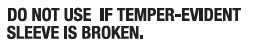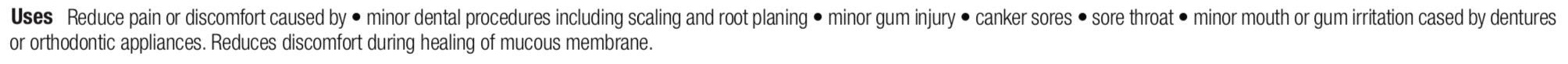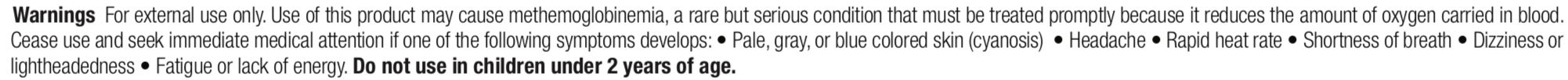 DRUG LABEL: GingiCaine Fusion
NDC: 10129-041 | Form: GEL
Manufacturer: Gingi-Pak a Division of the Belport
Category: otc | Type: HUMAN OTC DRUG LABEL
Date: 20211207

ACTIVE INGREDIENTS: BENZOCAINE 20 g/100 g
INACTIVE INGREDIENTS: POLYETHYLENE GLYCOL 3350 24 g/100 g; CANNABIDIOL 2 g/100 g; POLYETHYLENE GLYCOL 400 52 g/100 g; POTASSIUM SODIUM SACCHARATE 2 g/100 g

GingiCaine Fusion

RECENT MAJOR CHANGES

- Indications section was NOT modified and remains the same as the previous label
- Contraindications section was modified, such that the statement "do not use product for teething or in infants and children younger than 2" was added. This change was made effective on 12/07/2021.
- Caution section was modified, such that the previous statement was replaced with "store between 15 C (59 F) and 40 C (104 F).
- Uses section was madified, such that the statement "Reduces discomfort during healing process of mucous membrane," was added to pervious statement, effective 12/07/2021
- Warning section was modified, such that the defenition of methemoglobinemia is added to the statement, effective 12/07/2021.
- Jar Box_Strawberry, Jar Box_Vanilla, Jar Label_Strawberry, Jar label_Vanilla, Syringe_Strawberry, and Syringe_Vanilla sections were all updated with new label corrections, effective 12/07/2021